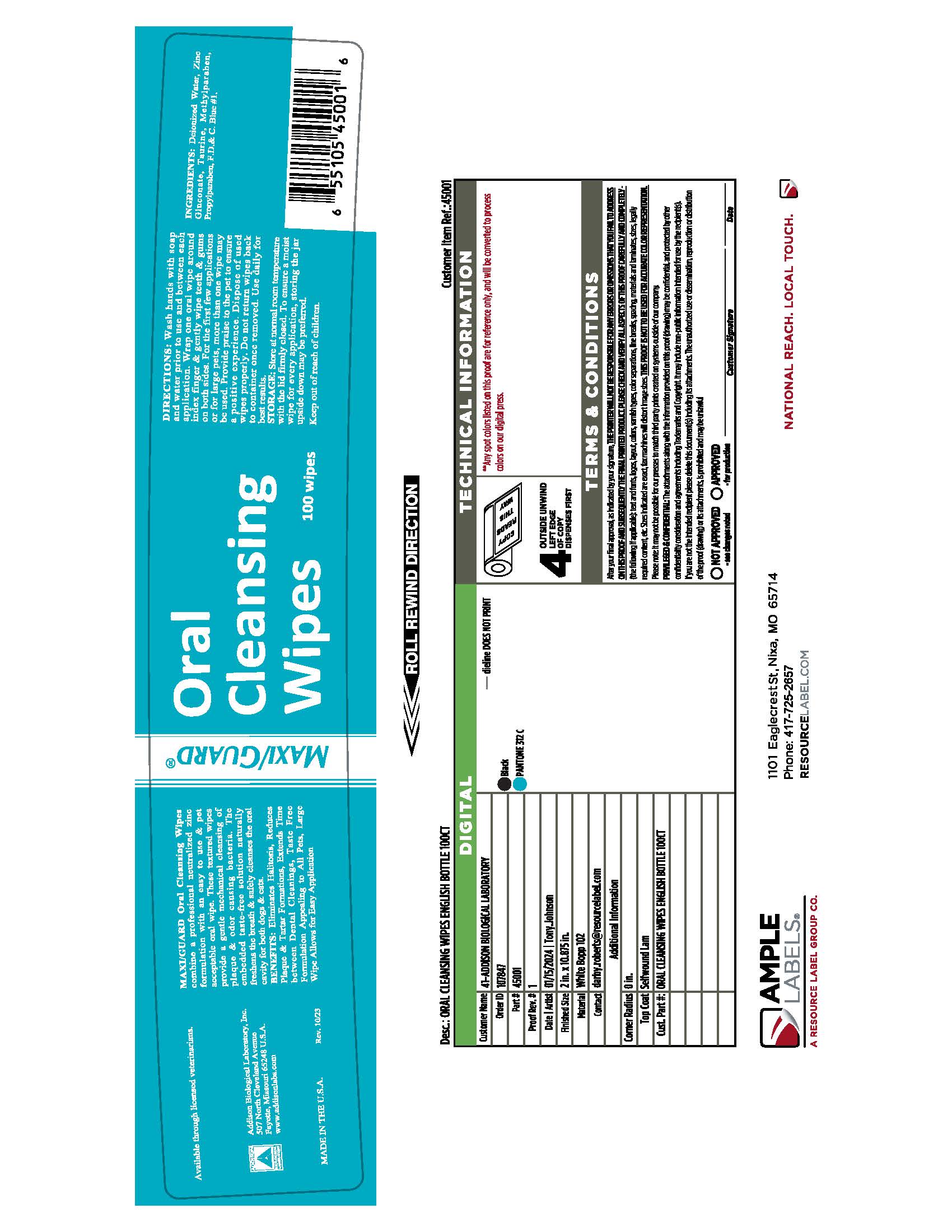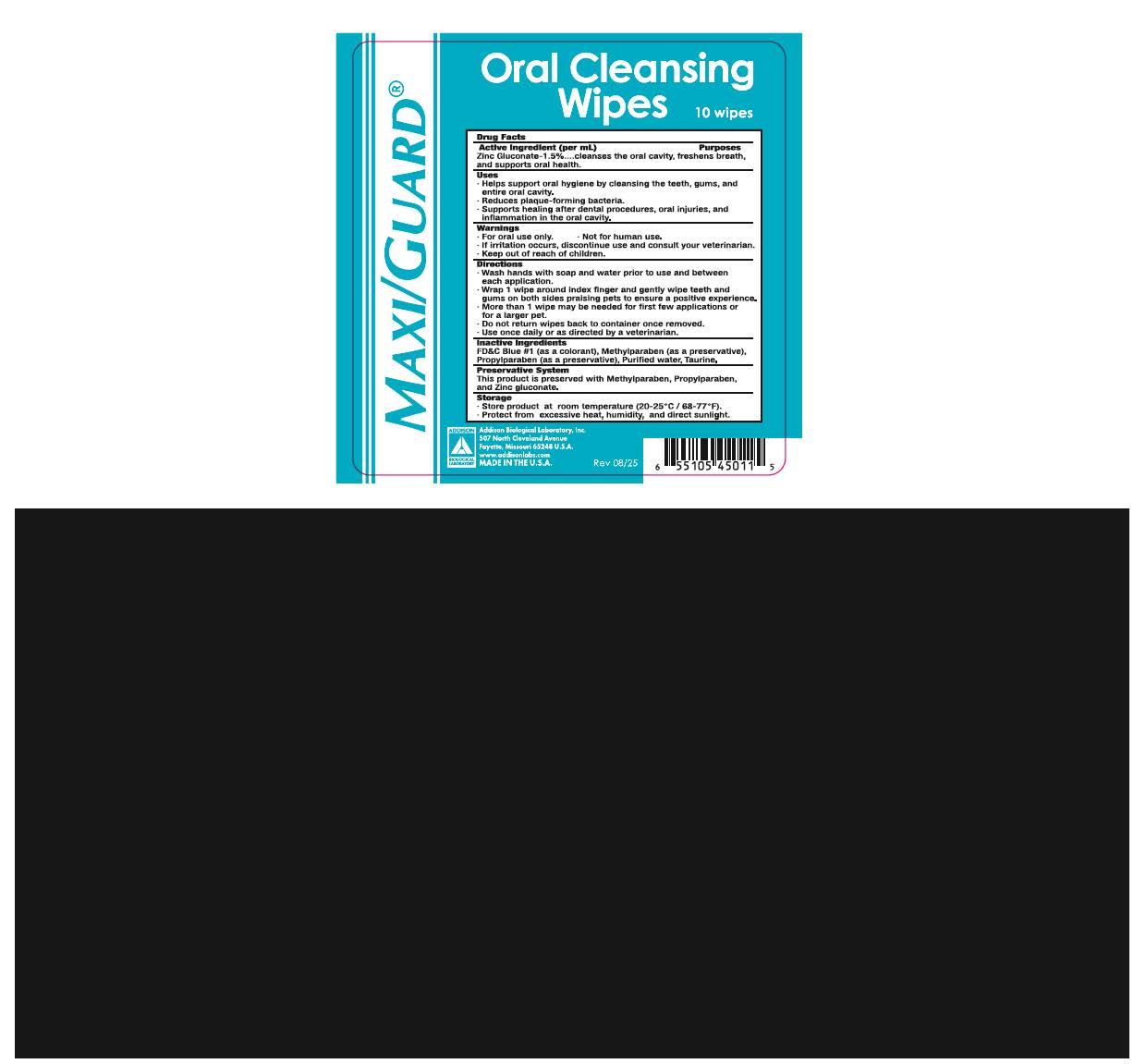 DRUG LABEL: Maxi/Guard Oral Cleansing Wipes
NDC: 86045-8100 | Form: SOLUTION
Manufacturer: Addison Biological Laboratory, Inc.
Category: animal | Type: OTC ANIMAL DRUG LABEL
Date: 20251218

ACTIVE INGREDIENTS: ZINC GLUCONATE .0165 1/1 1
INACTIVE INGREDIENTS: WATER; TAURINE; METHYLPARABEN; PROPYLPARABEN; FD&C BLUE NO. 1

Maxi/Guard Oral Cleansing Wipes

ACTIVE INGREDIENTS

Zinc gluconate-1.5%...cleanses the oral cavity,freshens breath, and supports oral health.

USES

- Helps support oral hygiene by cleansing the teeth, gums and entire oral cavity.
- Reduces plaque-forming bacteria.
- Supports healing after dental procedures, oral injuries, and inflammation in the oral cavity.

WARNINGS

- For oral use only. Not for human use.
- If irritation occurs, discontinue use and consult your veterinarian.
- Keep out of reach of children.

DIRECTIONS

- Wash hands with soap and water prior to use and between each application.
- Wrap 1 oral wipe around index finger & gently wipe teeth & gums on both sides praising pets to ensure a positive experience.
- More than 1 wipe may be needed for first few applications or larger pet.
- Do not return wipes back to container once removed.
- Use once daily oras directed by a veterinarian.

INACTIVE INGREDIENTS

FD & C Blue #1 (as colorant), Methylparaben (as a preservative), Propylparaben (as a preservative), Purified water, Taurine.

PRESERVATIVE SYSTEM

This product is preserved with Methylparaben, Propylparaben and Zinc gluconate.

STORAGE

- Store product at room temperature (20-25°C/68-77°F).
- Protect from excessive heat, humidity, and direct sunlight.

Addison Biological Laboratory, Inc.

507 North Cleveland Avenue Fayette, Missouri 65248 USA

www.addisonlabs.com

MADE IN THE U.S.A.

Rev. 08/25

Maxi/Guard Oral Cleansing Wipe 100 wipes

Maxi/Guard®

Oral Cleansing Wipes

Store product at room temperature (20-25°C/68-77°F).

Protect from excessive heat, humidity, and direct sunlight.

100 wipes

Drug Facts

Active Ingredient (per mL) Purposes

Zinc gluconate-1.5%...cleanses the oral cavity,freshens breath, and supports oral health.

Uses

- Helps support oral hygiene by cleansing the teeth, gums and entire oral cavity.
- Reduces plaque-forming bacteria.
- Supports healing after dental procedures, oral injuries, and inflammation in the oral cavity.

Warnings

- For oral use only. Not for human use.
- If irritation occurs, discontinue use and consult your veterinarian.
- Keep out of reach of children.

Directions

- Wash hands with soap and water prior to use and between each application.
- Wrap 1 oral wipe around index finger & gently wipe teeth & gums on both sides praising pets to ensure a positive experience.
- More than 1 wipe may be needed for first few applications or larger pet.
- Do not return wipes back to container once removed.
- Use once daily oras directed by a veterinarian.

Inactive Ingredients

FD & C Blue #1 (as colorant), Methylparaben (as a preservative), Propylparaben (as a preservative), Purified water, Taurine.

Preservative System

This product is preserved with Methylparaben, Propylparaben and Zinc gluconate.

Storage

- Store product at room temperature (20-25°C/68-77°F).
- Protect from excessive heat, humidity, and direct sunlight.

Addison Biological Laboratory, Inc.

507 North Cleveland Avenue Fayette, Missouri 65248 USA

www.addisonlabs.com

MADE IN THE U.S.A.

Rev. 10/25

Maxi/Guard Oral Cleansing Wipe 10 wipes

Maxi/Guard®

Oral Cleansing Wipes

Store product at room temperature (20-25°C/68-77°F).

Protect from excessive heat, humidity, and direct sunlight.

10 wipes

Drug Facts

Active Ingredient (per mL) Purposes

Zinc gluconate-1.5%...cleanses the oral cavity,freshens breath, and supports oral health.

Uses

- Helps support oral hygiene by cleansing the teeth, gums and entire oral cavity.
- Reduces plaque-forming bacteria.
- Supports healing after dental procedures, oral injuries, and inflammation in the oral cavity.

Warnings

- For oral use only. Not for human use.
- If irritation occurs, discontinue use and consult your veterinarian.
- Keep out of reach of children.

Directions

- Wash hands with soap and water prior to use and between each application.
- Wrap 1 oral wipe around index finger & gently wipe teeth & gums on both sides praising pets to ensure a positive experience.
- More than 1 wipe may be needed for first few applications or larger pet.
- Do not return wipes back to container once removed.
- Use once daily oras directed by a veterinarian.

Inactive Ingredients

FD & C Blue #1 (as colorant), Methylparaben (as a preservative), Propylparaben (as a preservative), Purified water, Taurine.

Preservative System

This product is preserved with Methylparaben, Propylparaben and Zinc gluconate.

Storage

- Store product at room temperature (20-25°C/68-77°F).
- Protect from excessive heat, humidity, and direct sunlight.

Addison Biological Laboratory, Inc.

507 North Cleveland Avenue Fayette, Missouri 65248 USA

www.addisonlabs.com

MADE IN THE U.S.A.

Rev. 10/25